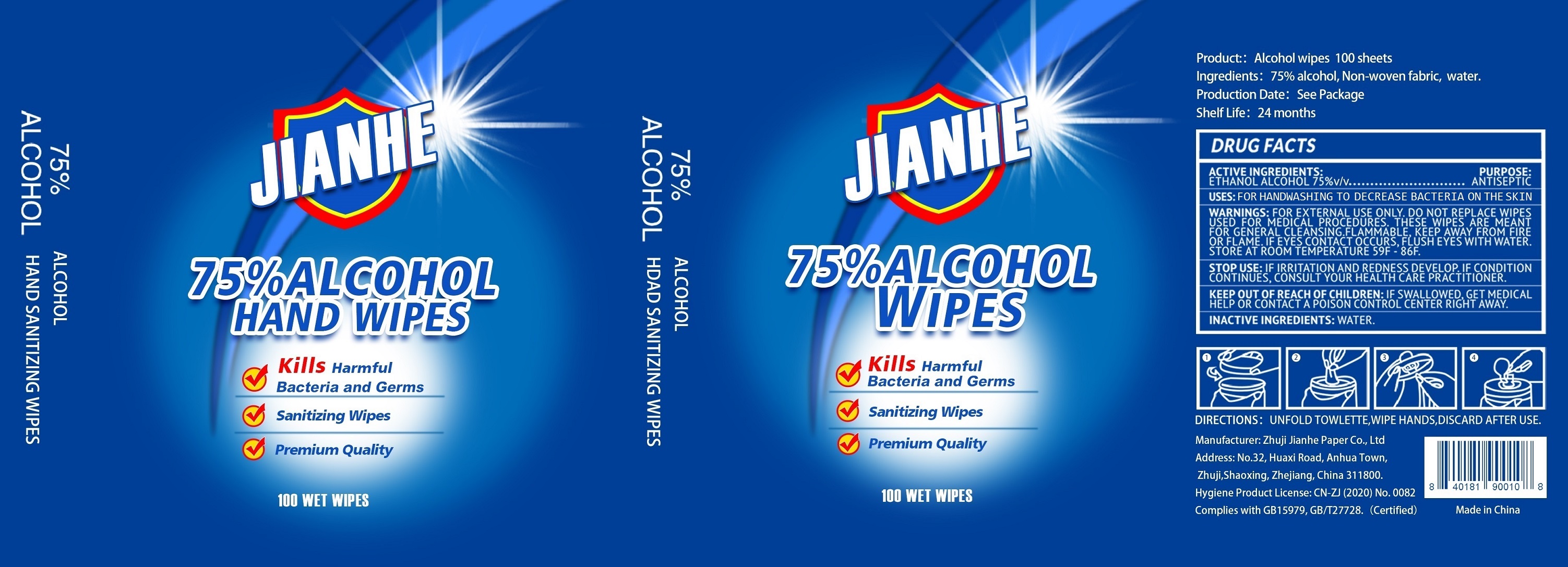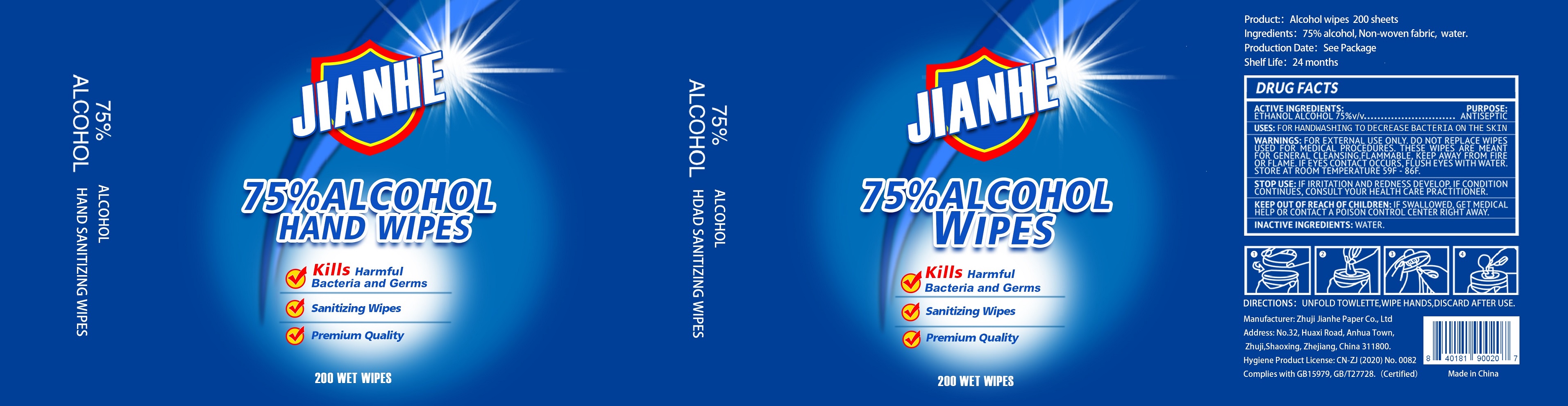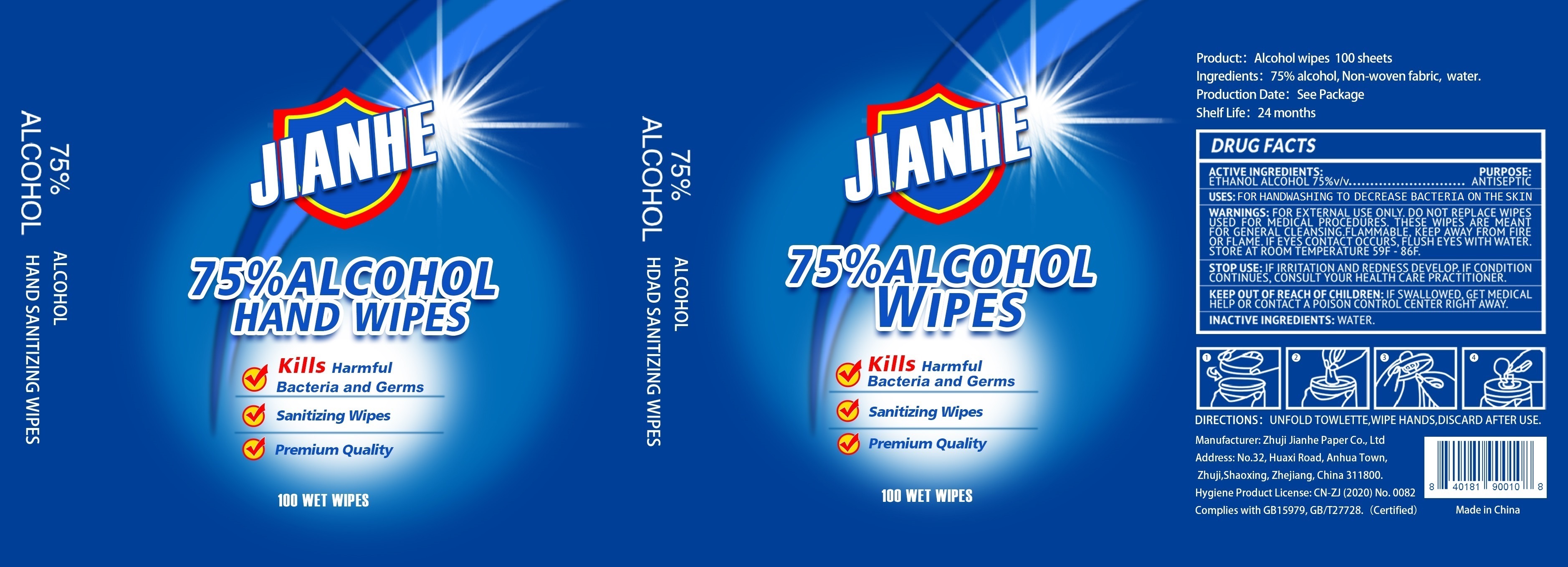 DRUG LABEL: ALCOHOL WIPES
NDC: 75163-003 | Form: CLOTH
Manufacturer: Zhuji Jianhe Paper Co., Ltd
Category: otc | Type: HUMAN OTC DRUG LABEL
Date: 20200920

ACTIVE INGREDIENTS: ALCOHOL 0.75 U/1 U
INACTIVE INGREDIENTS: WATER

75163-003 100 PAIL 200 PAIL jinahe

Active Ingredient(s)

Alcohol 75% v/v. Purpose: Antiseptic

Inactive ingredients

Water

Purpose

ANTISEPTIC;

WHEN USING

THESE WIPES ARE MEANT FOR GENERAL CLEANSING.

Do not use

DO NOT REPLACE WIPES USED FOR MEDICAL PROCEDURES.

STOP USE: IF IRRITATION AND REDNESS DEVELOP. IFCONDITION CONTINUS, CONSULT YOUR HEALTH CARE PRACTITIONER.

KEEP OUT OF REACH OF CHILDREN: IF SWALLOWED, GET MEDICAL HELP OR CONTACT A POISON CONTROL CENTER RIGHT AWAY.

Use

FOR HANDWASHING TO DECREASE BACTERIA ON THE SKIN.

Directions

DIRECTIONS: UNFOLD TOWLETTE, WIPE HANDS, DISCARD AFTER USE.

Warnings

FOR EXTERNAL USE ONLY. DO NOT REPLACE WIPES USED FOR MEDICAL PROCEDURES. THESE WIPES ARE MEANT FOR GENERAL CLEANSING. FLAMMABLE, KEEP AWAY FROM FIRE OR FLAME. IF EYES CONTACT OCCURS, FLUSH EYES WITH WATER. STORE AT ROOM TEMPERATURE 59F - 86 F.

Other information

- STORE AT ROOM TEMPERATURE 59F - 86F.

Package Label - Principal Display Panel

100 U 1 PAIL NDC:75163-003-01

200 U 1 PAIL NDC:75163-003-02